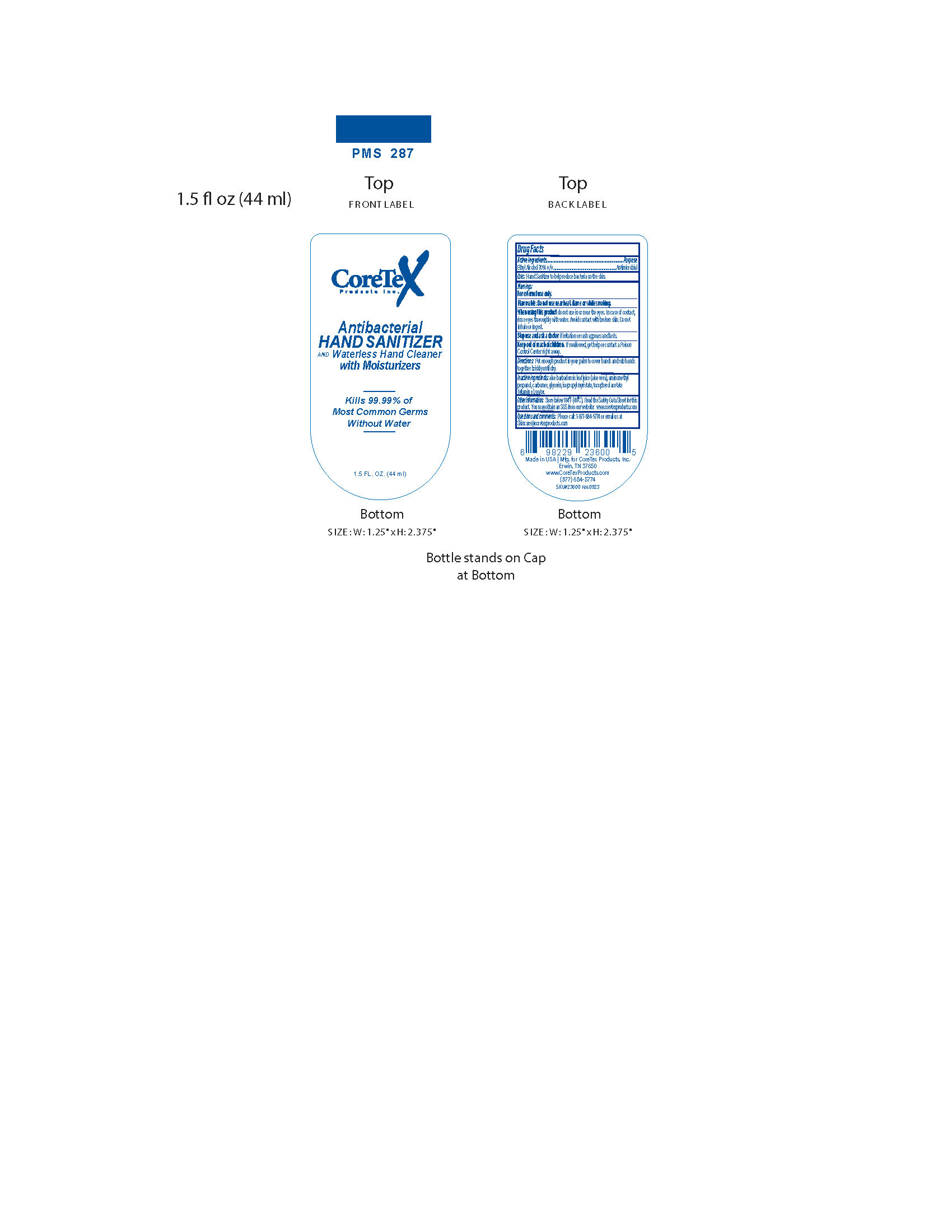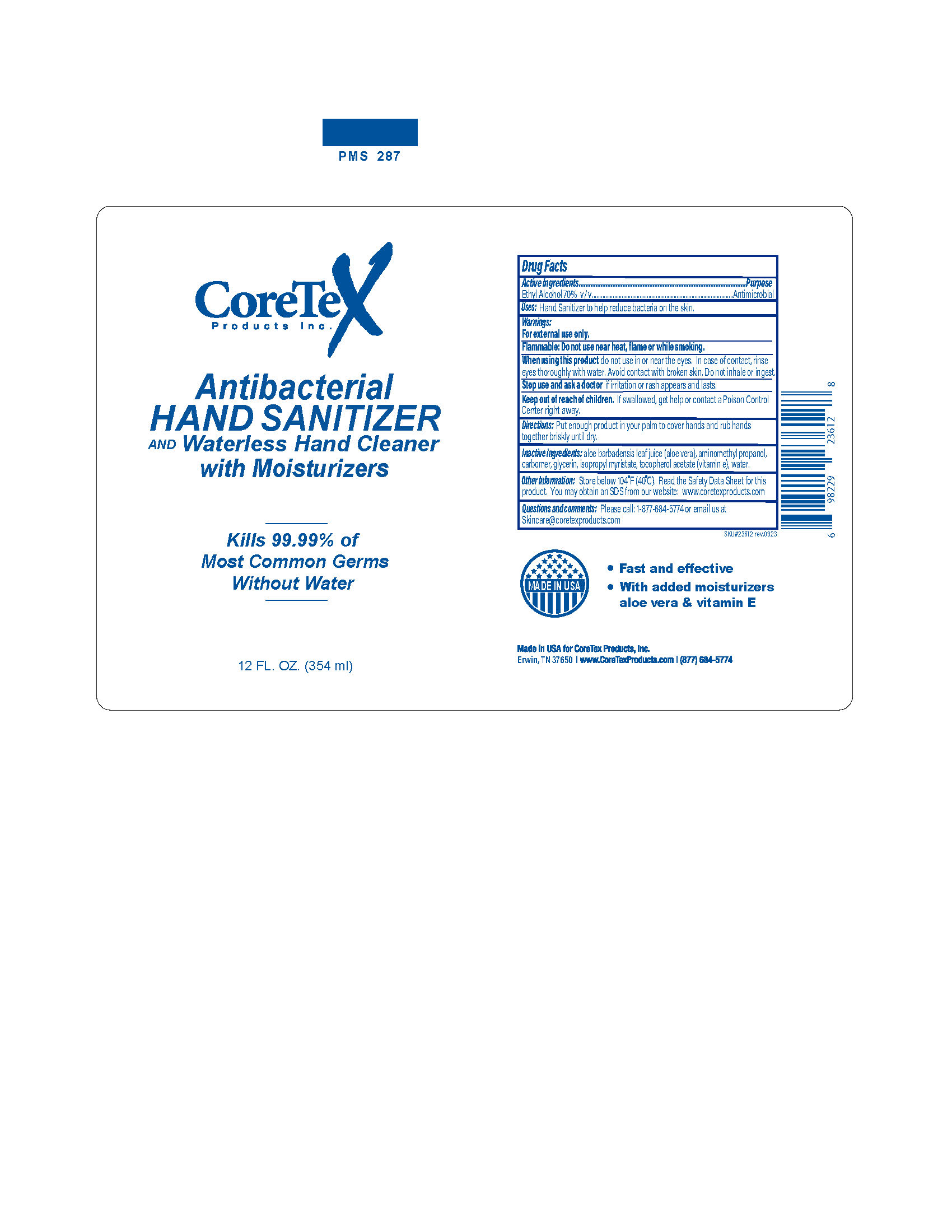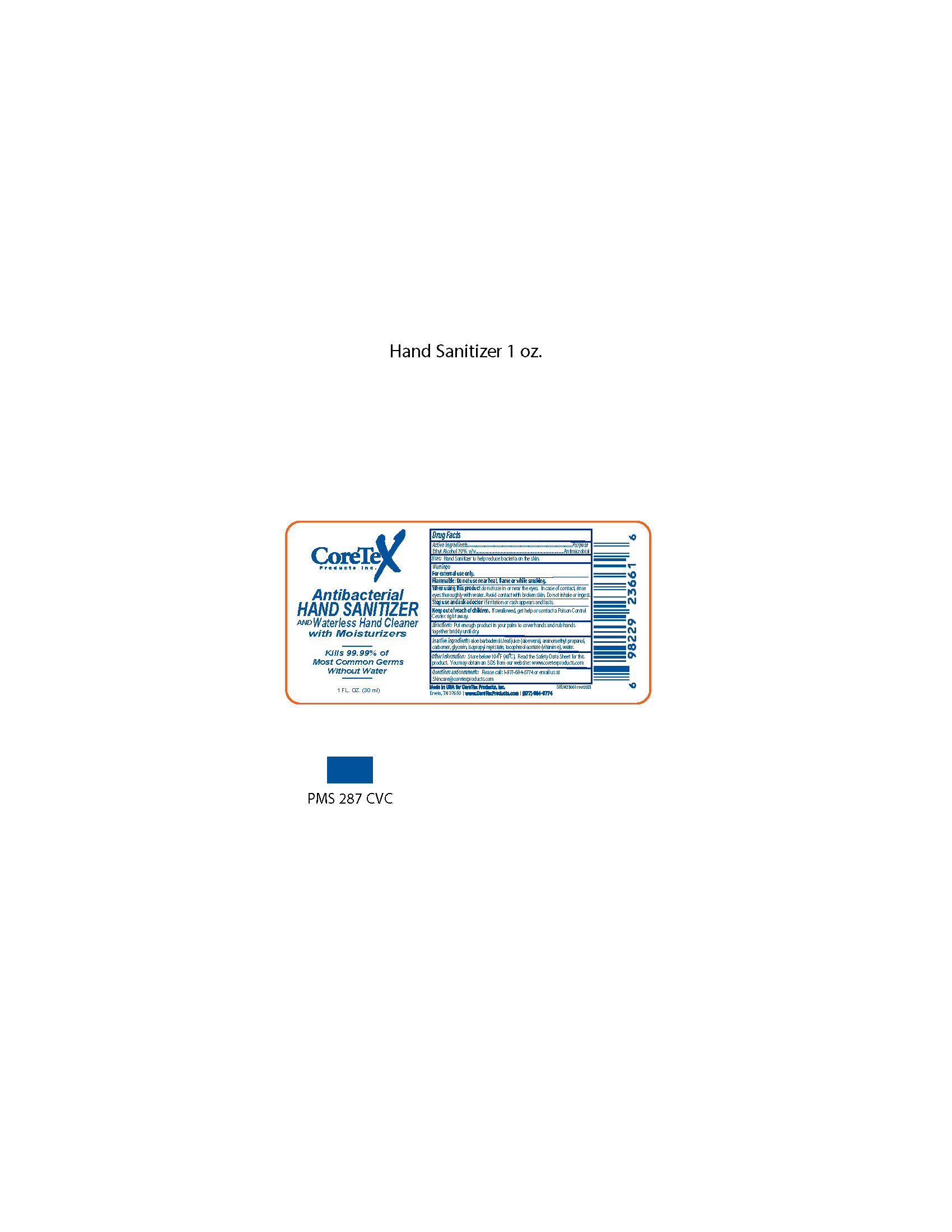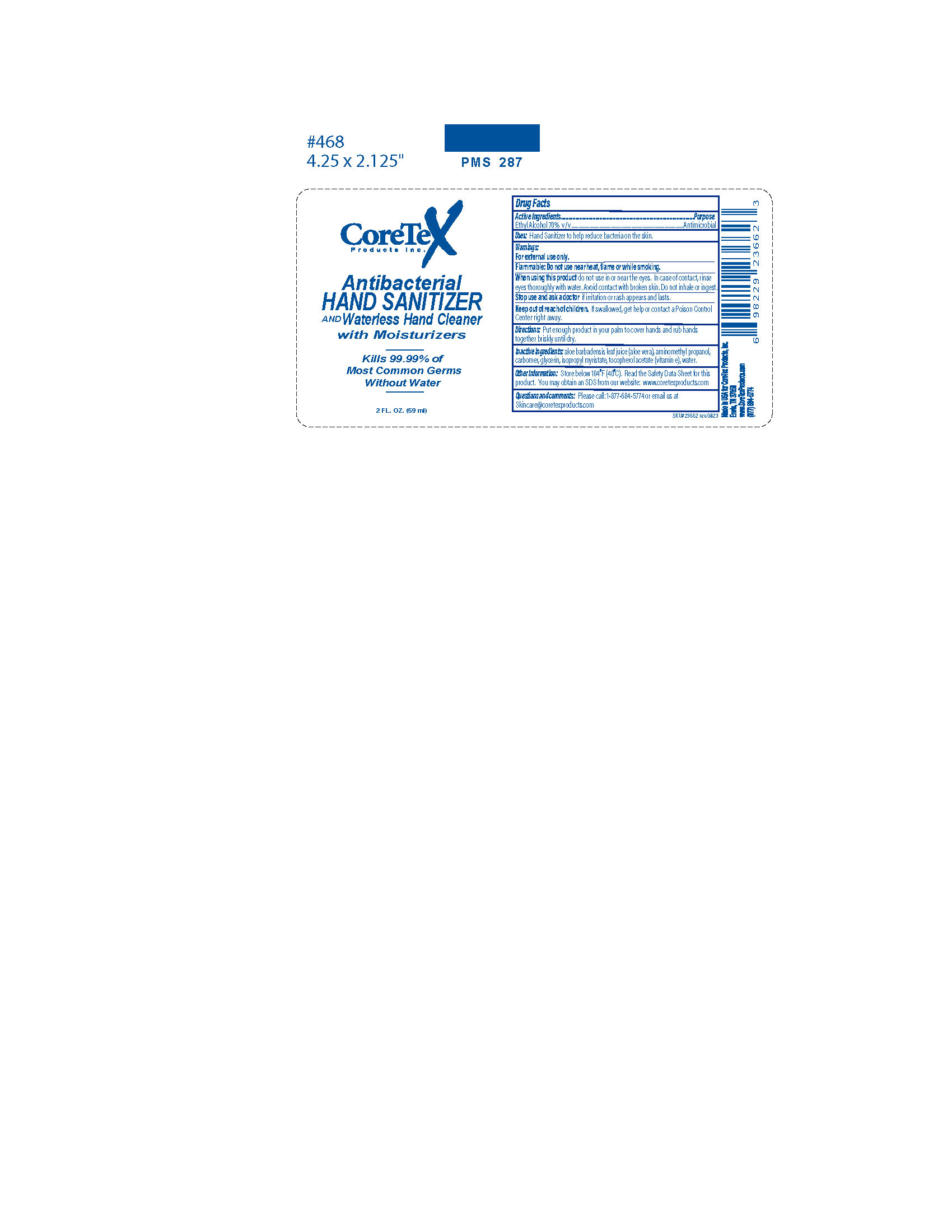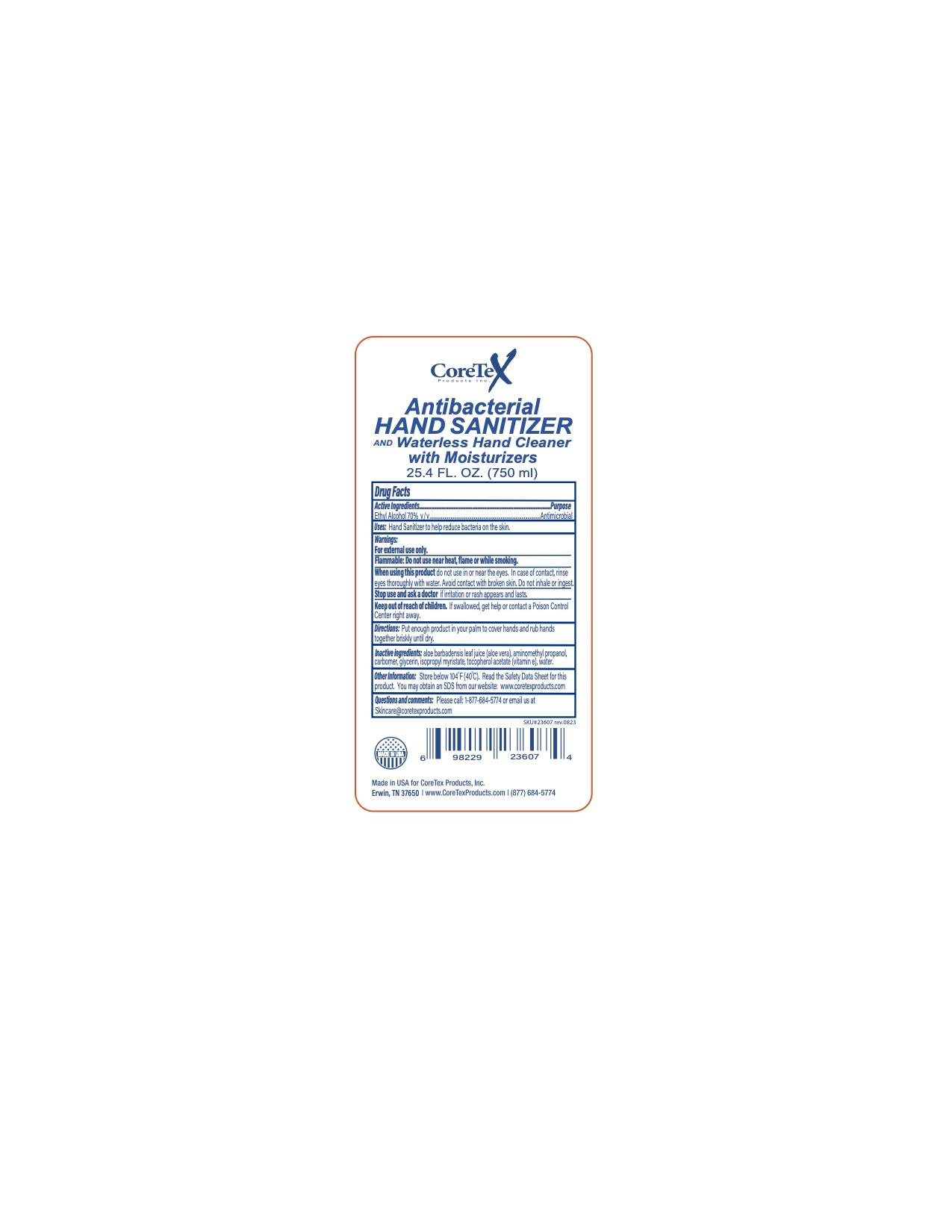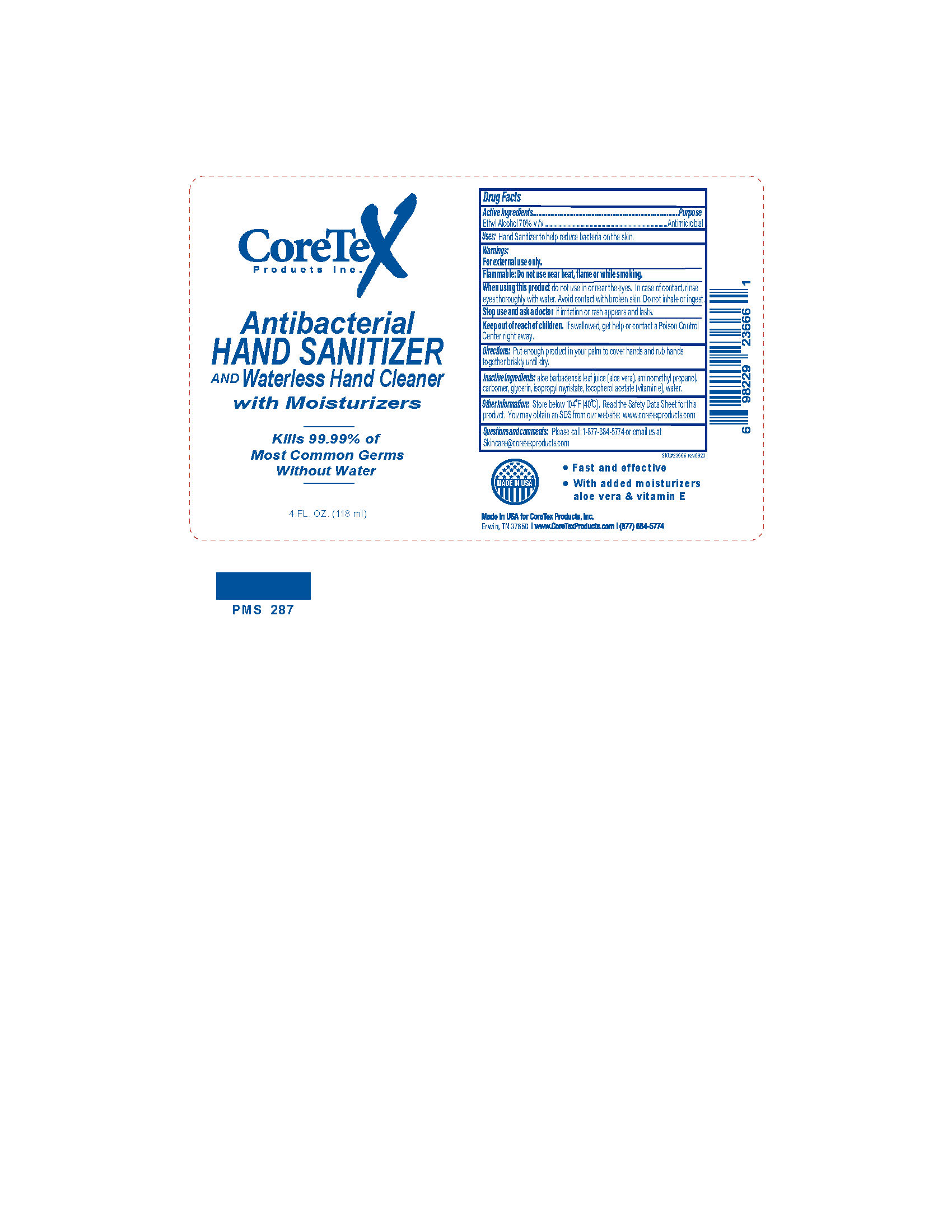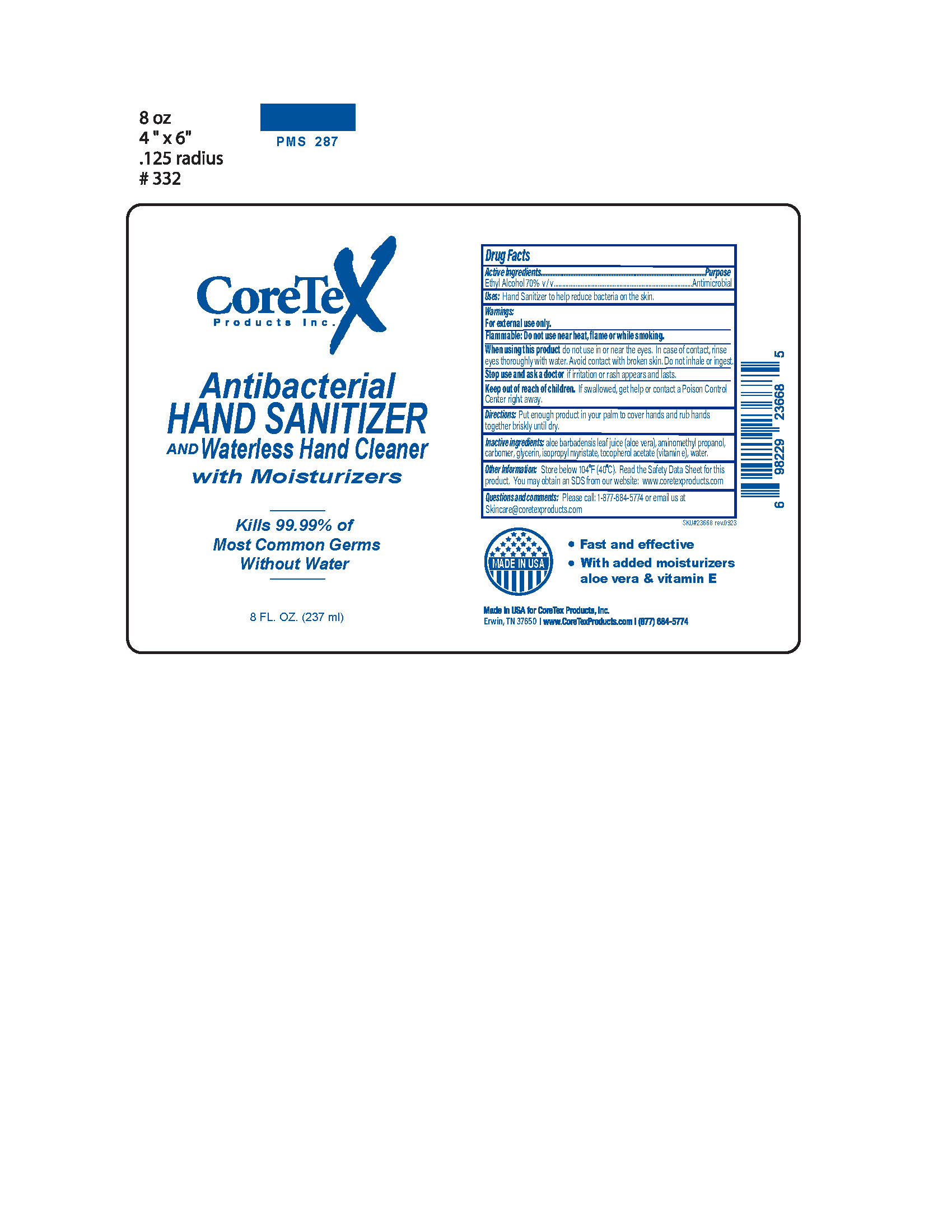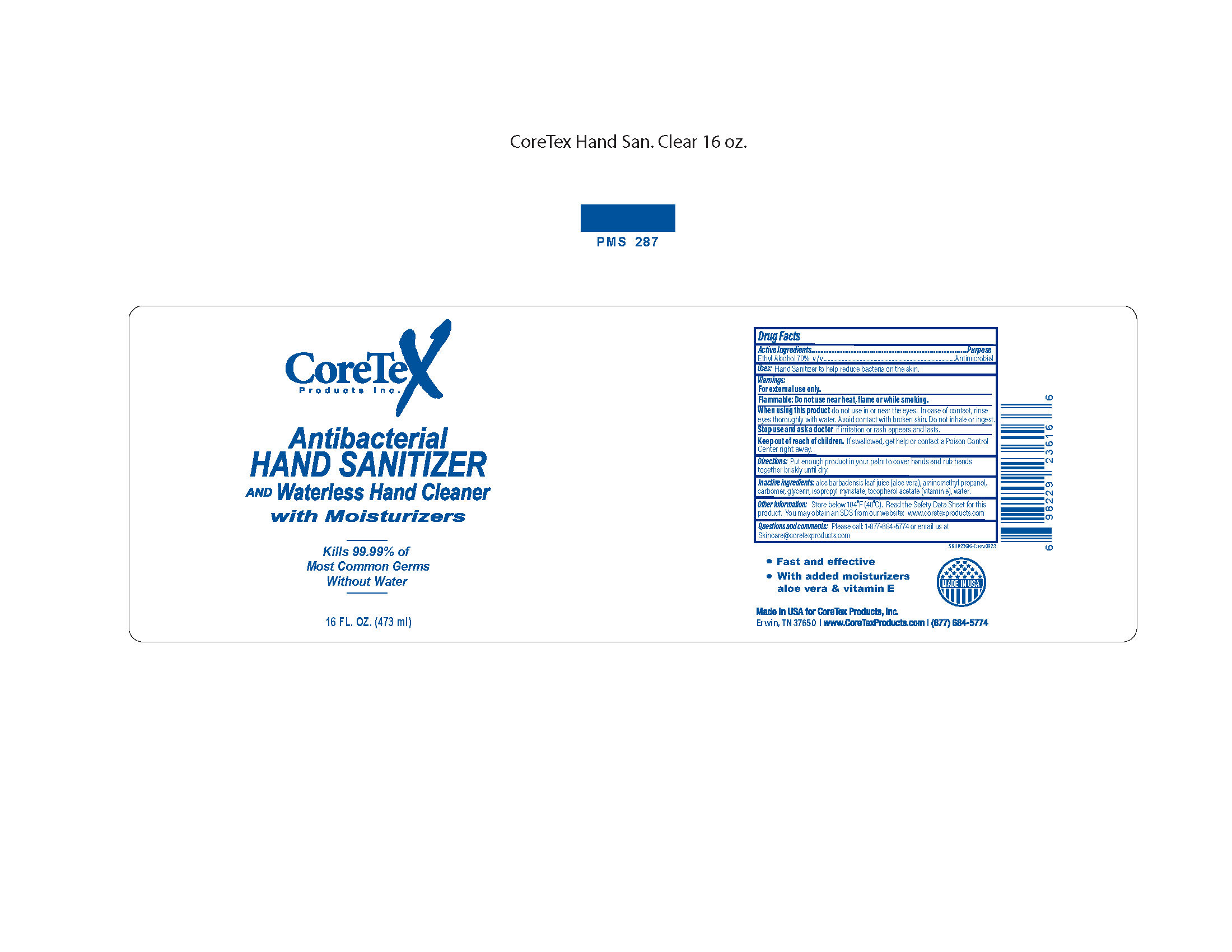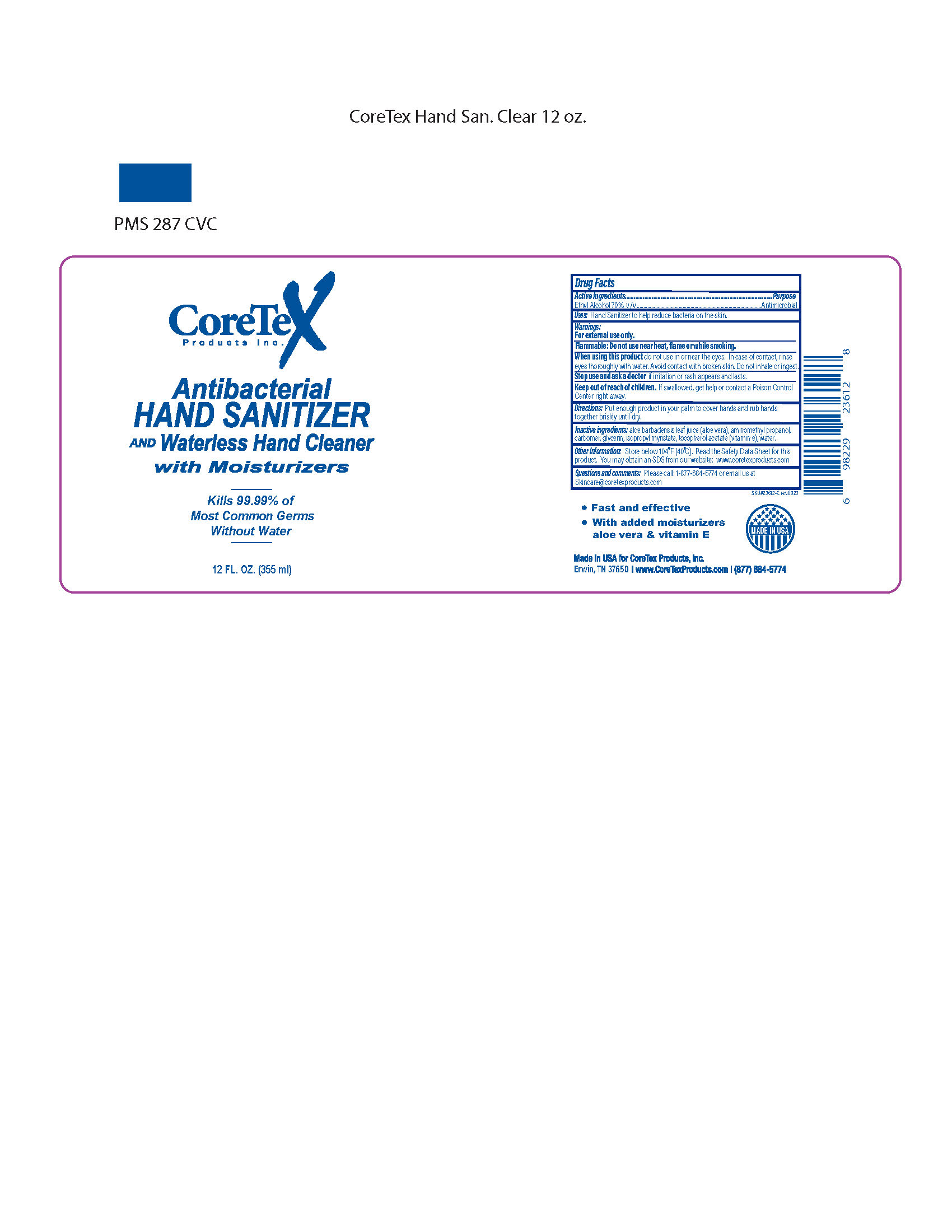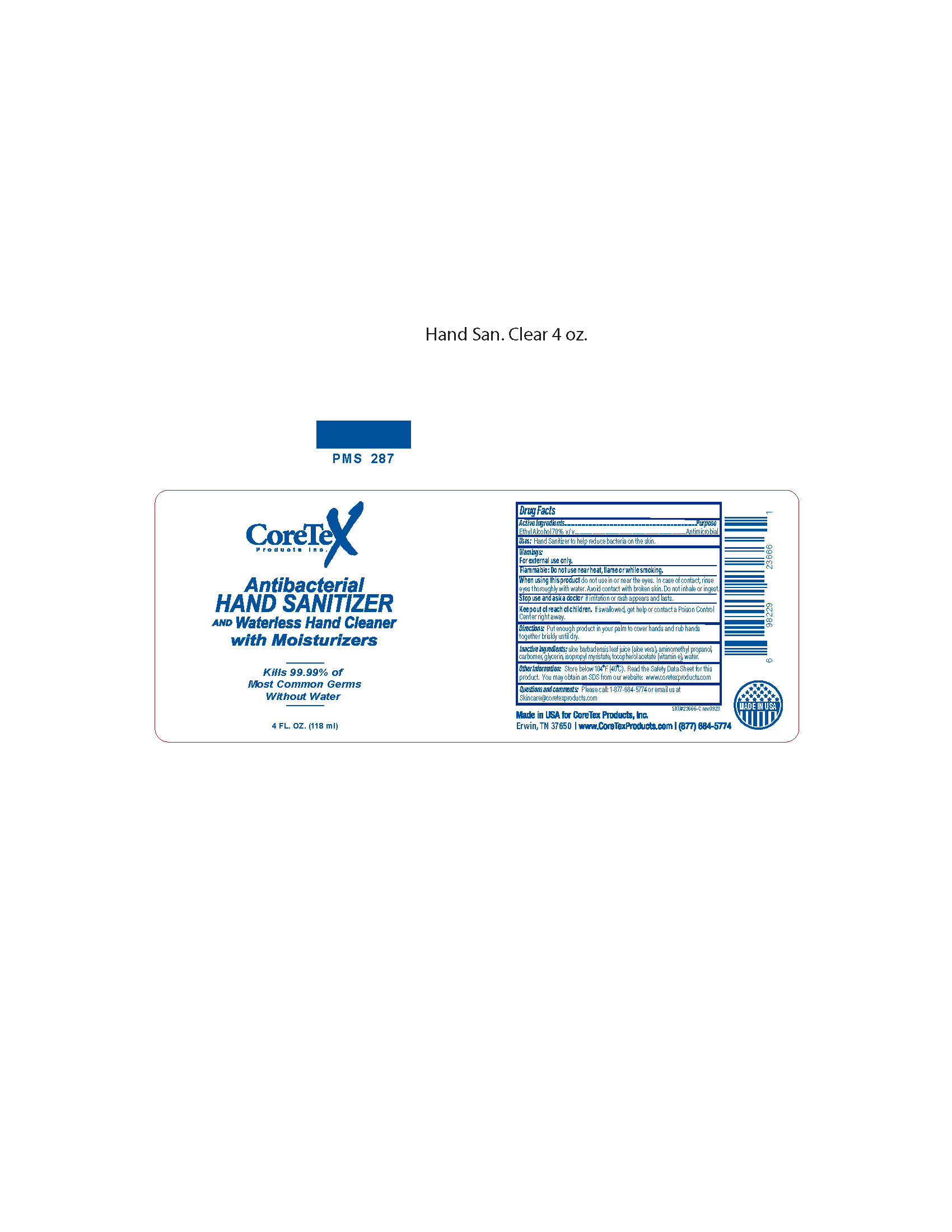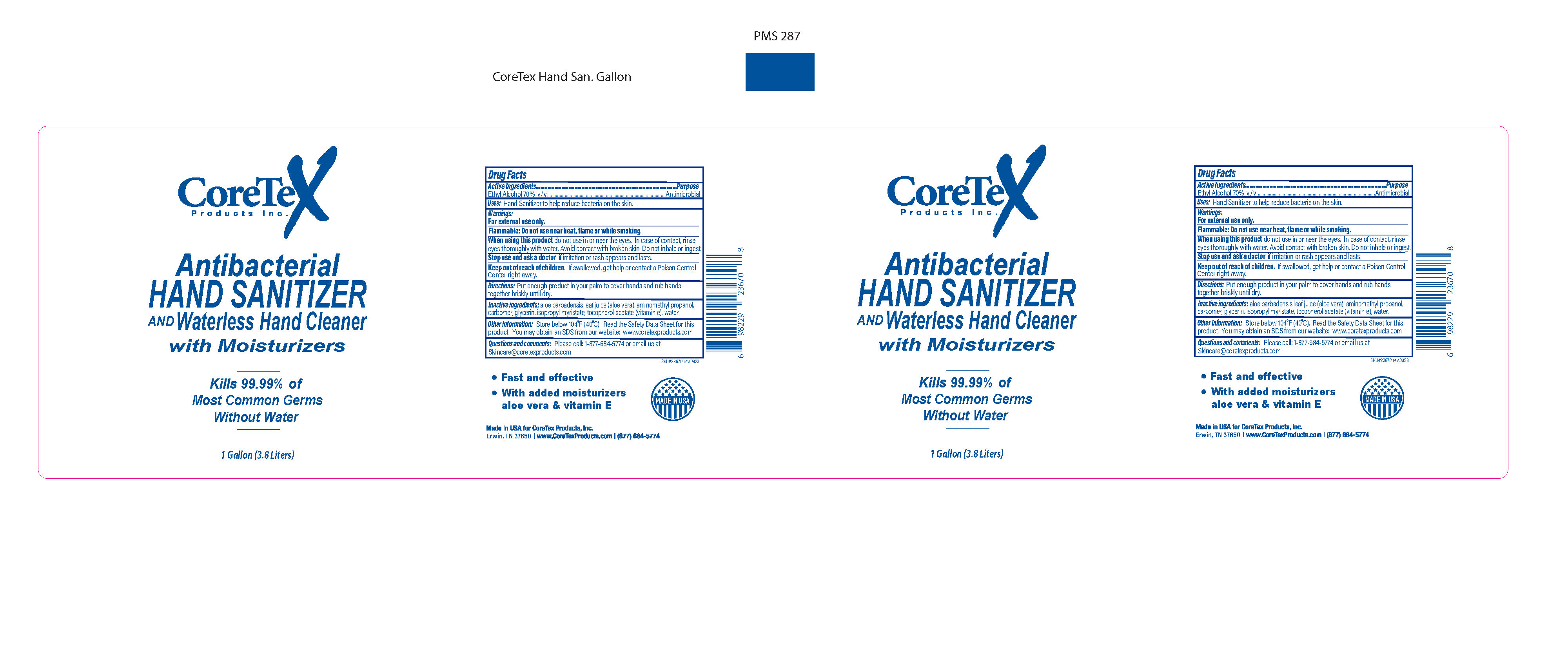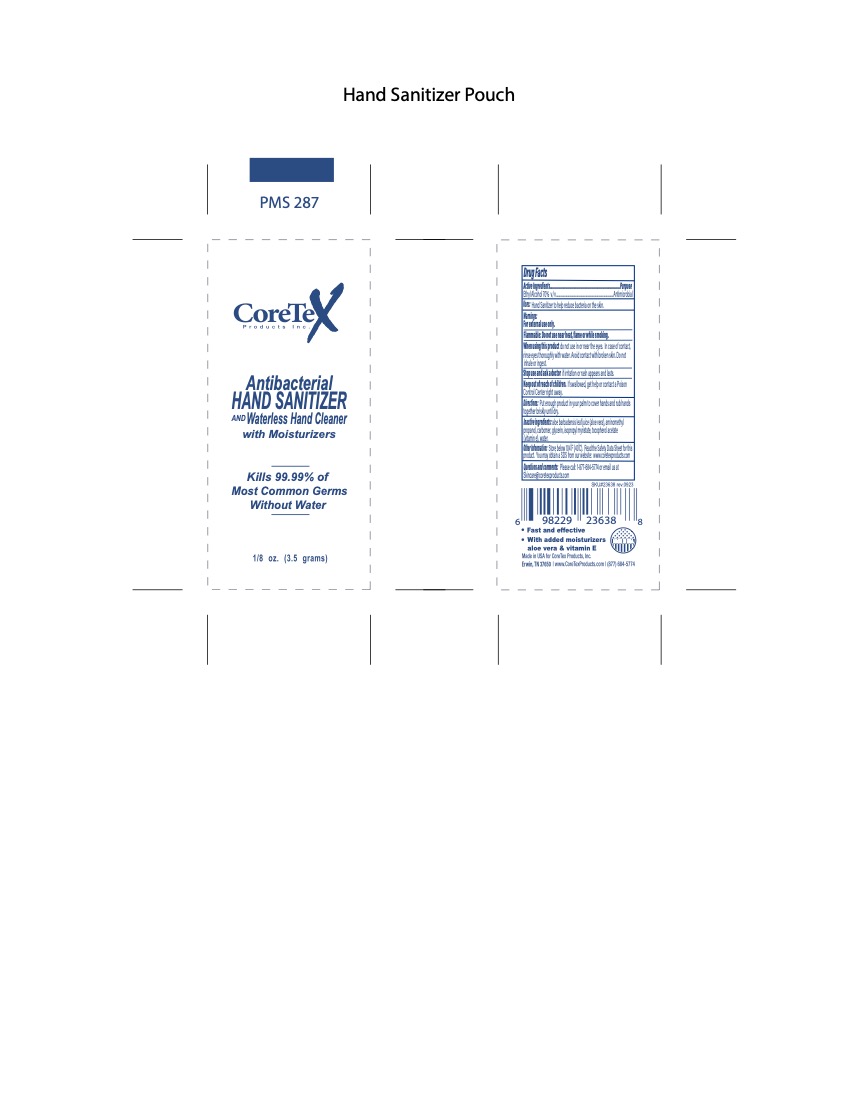 DRUG LABEL: CoreTex Antibacterial Hand Sanitizer
NDC: 65753-201 | Form: LIQUID
Manufacturer: CoreTex Products Inc
Category: otc | Type: HUMAN OTC DRUG LABEL
Date: 20241202

ACTIVE INGREDIENTS: ALCOHOL 70 mL/100 mL
INACTIVE INGREDIENTS: CARBOMER HOMOPOLYMER, UNSPECIFIED TYPE; ALOE VERA LEAF; AMINOMETHYL PROPANEDIOL; GLYCERIN; ISOPROPYL MYRISTATE; WATER; ALPHA-TOCOPHEROL ACETATE

CoreTex Antibacterial Hand Sanitizer
65753-201

Active Ingredients

Ethyl Alcohol 70% v/v

Purpose

Antimicrobial

Uses:

Hand Sanitizer to help reduce bacteria on the skin.

Warnings:

For external use only.

Flammable. Do not use near heat, flame or while smoking.

When using this product

do not use in or near the eyes. In case of contact, rinse eyes thoroughly with water. Avoid contact with broken skin. Do not inhale or ingest.

Stop use and ask a doctor

if irritation or rash appears and lasts.

Keep out of reach of children.

If swallowed, get help or contact a Poison Control Center right away.

Directions:

Put enough product in your palm to cover hands and rub hands together briskly until dry.

Inactive Ingredients:

aloe barbadenis leaf juice(aloe vera), amino methylpropanol, carbomer, glycerin, isopropyl myristate, tocopherol acetate (vitamin E acetate), water

Other Information:

Store below 104oF (40oC), Read the Safety Data Sheet for this Product. You may obtain an SDS from our website: www.coretexproducts.com

Questions and comments:

Please call: 1-877-684-5774 or email us at Skincare@coretexproducts.com

Made in USA for CoreTex Products, Inc.

Erwin, TN 37650 |www.CoreTexProducts.com | (877) 684-5774